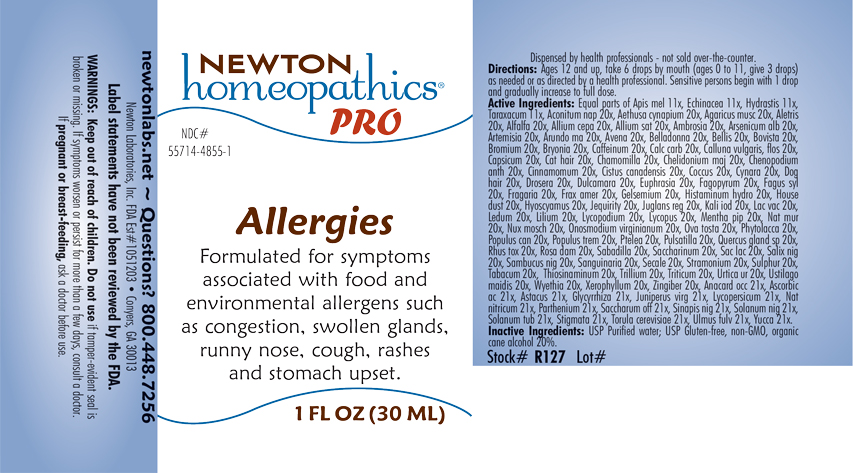 DRUG LABEL: Allergies
NDC: 55714-4855 | Form: LIQUID
Manufacturer: Newton Laboratories, Inc.
Category: homeopathic | Type: HUMAN OTC DRUG LABEL
Date: 20230925

ACTIVE INGREDIENTS: ULMUS RUBRA BARK 21 [hp_X]/1 mL; EGG SHELL, COOKED 20 [hp_X]/1 mL; SCHOENOCAULON OFFICINALE SEED 20 [hp_X]/1 mL; SAMBUCUS NIGRA FLOWERING TOP 20 [hp_X]/1 mL; SANGUINARIA CANADENSIS ROOT 20 [hp_X]/1 mL; LYCOPUS VIRGINICUS 20 [hp_X]/1 mL; LACTOSE, UNSPECIFIED FORM 20 [hp_X]/1 mL; CLAVICEPS PURPUREA SCLEROTIUM 20 [hp_X]/1 mL; TRILLIUM ERECTUM ROOT 20 [hp_X]/1 mL; ASCORBIC ACID 21 [hp_X]/1 mL; BLACK MUSTARD SEED 21 [hp_X]/1 mL; DATURA STRAMONIUM 20 [hp_X]/1 mL; TOBACCO LEAF 20 [hp_X]/1 mL; ALLYLTHIOUREA 20 [hp_X]/1 mL; URTICA URENS 20 [hp_X]/1 mL; ELYMUS REPENS ROOT 20 [hp_X]/1 mL; USTILAGO MAYDIS 20 [hp_X]/1 mL; WYETHIA HELENIOIDES ROOT 20 [hp_X]/1 mL; XEROPHYLLUM ASPHODELOIDES 20 [hp_X]/1 mL; APIS MELLIFERA 11 [hp_X]/1 mL; TARAXACUM OFFICINALE 11 [hp_X]/1 mL; ACONITUM NAPELLUS 20 [hp_X]/1 mL; AETHUSA CYNAPIUM 20 [hp_X]/1 mL; AMANITA MUSCARIA FRUITING BODY 20 [hp_X]/1 mL; ALETRIS FARINOSA ROOT 20 [hp_X]/1 mL; ALFALFA 20 [hp_X]/1 mL; ONION 20 [hp_X]/1 mL; GARLIC 20 [hp_X]/1 mL; AMBROSIA ARTEMISIIFOLIA 20 [hp_X]/1 mL; ARSENIC TRIOXIDE 20 [hp_X]/1 mL; ARTEMISIA VULGARIS ROOT 20 [hp_X]/1 mL; ARUNDO PLINIANA ROOT 20 [hp_X]/1 mL; AVENA SATIVA FLOWERING TOP 20 [hp_X]/1 mL; ATROPA BELLADONNA 20 [hp_X]/1 mL; BELLIS PERENNIS 20 [hp_X]/1 mL; LYCOPERDON UTRIFORME FRUITING BODY 20 [hp_X]/1 mL; BROMINE 20 [hp_X]/1 mL; BRYONIA ALBA ROOT 20 [hp_X]/1 mL; CAFFEINE 20 [hp_X]/1 mL; OYSTER SHELL CALCIUM CARBONATE, CRUDE 20 [hp_X]/1 mL; CALLUNA VULGARIS FLOWERING TOP 20 [hp_X]/1 mL; CAPSICUM 20 [hp_X]/1 mL; FELIS CATUS HAIR 20 [hp_X]/1 mL; MATRICARIA CHAMOMILLA 20 [hp_X]/1 mL; CHELIDONIUM MAJUS 20 [hp_X]/1 mL; DYSPHANIA AMBROSIOIDES 20 [hp_X]/1 mL; CINNAMON 20 [hp_X]/1 mL; HELIANTHEMUM CANADENSE 20 [hp_X]/1 mL; PROTORTONIA CACTI 20 [hp_X]/1 mL; CYNARA SCOLYMUS LEAF 20 [hp_X]/1 mL; CANIS LUPUS FAMILIARIS HAIR 20 [hp_X]/1 mL; DROSERA ANGLICA 20 [hp_X]/1 mL; SOLANUM DULCAMARA TOP 20 [hp_X]/1 mL; EUPHRASIA STRICTA 20 [hp_X]/1 mL; FAGOPYRUM ESCULENTUM 20 [hp_X]/1 mL; FAGUS SYLVATICA NUT 20 [hp_X]/1 mL; ALPINE STRAWBERRY 20 [hp_X]/1 mL; FRAXINUS AMERICANA BARK 20 [hp_X]/1 mL; GELSEMIUM SEMPERVIRENS ROOT 20 [hp_X]/1 mL; HISTAMINE DIHYDROCHLORIDE 20 [hp_X]/1 mL; HOUSE DUST 20 [hp_X]/1 mL; HYOSCYAMUS NIGER 20 [hp_X]/1 mL; ABRUS PRECATORIUS SEED 20 [hp_X]/1 mL; JUGLANS REGIA LEAF 20 [hp_X]/1 mL; POTASSIUM IODIDE 20 [hp_X]/1 mL; COW MILK 20 [hp_X]/1 mL; RHODODENDRON TOMENTOSUM LEAFY TWIG 20 [hp_X]/1 mL; LILIUM LANCIFOLIUM WHOLE FLOWERING 20 [hp_X]/1 mL; ONOSMODIUM VIRGINIANUM 20 [hp_X]/1 mL; PHYTOLACCA AMERICANA ROOT 20 [hp_X]/1 mL; YUCCA FILAMENTOSA 21 [hp_X]/1 mL; SACCHARIN 20 [hp_X]/1 mL; ECHINACEA, UNSPECIFIED 11 [hp_X]/1 mL; GOLDENSEAL 11 [hp_X]/1 mL; TOXICODENDRON PUBESCENS LEAF 20 [hp_X]/1 mL; SALIX NIGRA BARK 20 [hp_X]/1 mL; SULFUR 20 [hp_X]/1 mL; POPULUS BALSAMIFERA LEAF BUD 20 [hp_X]/1 mL; QUERCUS ROBUR NUT 20 [hp_X]/1 mL; MENTHA PIPERITA 20 [hp_X]/1 mL; NUTMEG 20 [hp_X]/1 mL; SOLANUM LYCOPERSICUM 21 [hp_X]/1 mL; ANACARDIUM OCCIDENTALE FRUIT 21 [hp_X]/1 mL; PTELEA TRIFOLIATA BARK 20 [hp_X]/1 mL; LYCOPODIUM CLAVATUM SPORE 20 [hp_X]/1 mL; ANEMONE PULSATILLA 20 [hp_X]/1 mL; ROSA X DAMASCENA FLOWERING TOP 20 [hp_X]/1 mL; ASTACUS ASTACUS 21 [hp_X]/1 mL; GLYCYRRHIZA GLABRA 21 [hp_X]/1 mL; JUNIPERUS VIRGINIANA TWIG 21 [hp_X]/1 mL; SUCROSE 21 [hp_X]/1 mL; SODIUM NITRATE 21 [hp_X]/1 mL; SOLANUM NIGRUM WHOLE 21 [hp_X]/1 mL; SOLANUM TUBEROSUM 21 [hp_X]/1 mL; PARTHENIUM HYSTEROPHORUS 21 [hp_X]/1 mL; GINGER 20 [hp_X]/1 mL; SODIUM CHLORIDE 20 [hp_X]/1 mL; POPULUS TREMULOIDES LEAF 20 [hp_X]/1 mL; CORN SILK 21 [hp_X]/1 mL; SACCHAROMYCES CEREVISIAE 21 [hp_X]/1 mL
INACTIVE INGREDIENTS: WATER; ALCOHOL

Allergies 4855L

INDICATIONS & USAGE SECTION

Formulated for symptoms associated with food and environmental allergens such as congestion, swollen glands, runny nose, cough, rashes and stomach upset.

DOSAGE & ADMINISTRATION SECTION

Directions: Ages 12 and up take 6 drops by mouth (ages 0 to 11, give 3 drops) as needed or directed by a health professional. Sensitive persons begin with 1 drop and gradually increase to full dose.

OTC - ACTIVE INGREDIENT SECTION

Equal parts of Apis mel 11x, Echinacea 11x, Hydrastis 11x, Taraxacum 11x, Aconitum nap 20x, Aethusa cynapium 20x, Agaricus musc 20x, Aletris 20x, Alfalfa 20x, Allium cepa 20x, Allium sat 20x, Ambrosia 20x, Arsenicum alb 20x, Artemisia 20x, Arundo ma 20x, Avena 20x, Belladonna 20x, Bellis 20x, Bovista 20x, Bromium 20x, Bryonia 20x, Caffeinum 20x, Calc carb 20x, Calluna vulgaris, flos 20x, Capsicum 20x, Cat hair 20x, Chamomilla 20x, Chelidonium maj 20x, Chenopodium anth 20x, Cinnamomum 20x, Cistus canadensis 20x, Coccus 20x, Cynara 20x, Dog hair 20x, Drosera 20x, Dulcamara 20x, Euphrasia 20x, Fagopyrum 20x, Fagus syl 20x, Fragaria 20x, Frax amer 20x, Gelsemium 20x, Histaminum hydro 20x, House dust 20x, Hyoscyamus 20x, Jequirity 20x, Juglans reg 20x, Kali iod 20x, Lac vac 20x, Ledum 20x, Lilium 20x, Lycopodium 20x, Lycopus 20x, Mentha pip 20x, Nat mur 20x, Nux mosch 20x, Onosmodium virginianum 20x, Ova tosta 20x, Phytolacca 20x, Populus can 20x, Populus trem 20x, Ptelea 20x, Pulsatilla 20x, Quercus gland sp 20x, Rhus tox 20x, Rosa dam 20x, Sabadilla 20x, Saccharinum 20x, Sac lac 20x, Salix nig 20x, Sambucus nig 20x, Sanguinaria 20x, Secale 20x, Stramonium 20x, Sulphur 20x, Tabacum 20x, Thiosinaminum 20x, Trillium 20x, Triticum 20x, Urtica ur 20x, Ustilago maidis 20x, Wyethia 20x, Xerophyllum 20x, Zingiber 20x, Anacardium occ 21x, Ascorbic ac 21x, Astacus 21x, Glycyrrhiza 21x, Juniperus virg 21x, Lycopersicum 21x, Nat nitricum 21x, Parthenium 21x, Saccharum off 21x, Sinapis nig 21x, Solanum nig 21x, Solanum tub 21x, Stigmata 21x, Torula cerevisiae 21x, Ulmus fulv 21x, Yucca 21x.

OTC - PURPOSE SECTION

Formulated for symptoms associated with food and environmental allergens such as congestion, swollen glands, runny nose, cough, rashes and stomach upset.

INACTIVE INGREDIENT SECTION

Inactive Ingredients: USP Purified Water; USP Gluten-free, non-GMO, organic cane alcohol 20%.

QUESTIONS SECTION

newtonlabs.net - Questions? 800.448.7256

Newton Laboratories, Inc. FDA Est # 1051203 Conyers, GA 30013

WARNINGS SECTION

WARNINGS: Keep out of reach of children. Do not use if tamper-evident seal is broken or missing. If symptoms worsen or persist for more than a few days, consult a doctor. If pregnant or breast-feeding, ask a doctor before use.

OTC - PREGNANCY OR BREAST FEEDING SECTION

If pregnant or breast-feeding, ask a doctor before use.

OTC - KEEP OUT OF REACH OF CHILDREN SECTION

Keep out of reach of children.